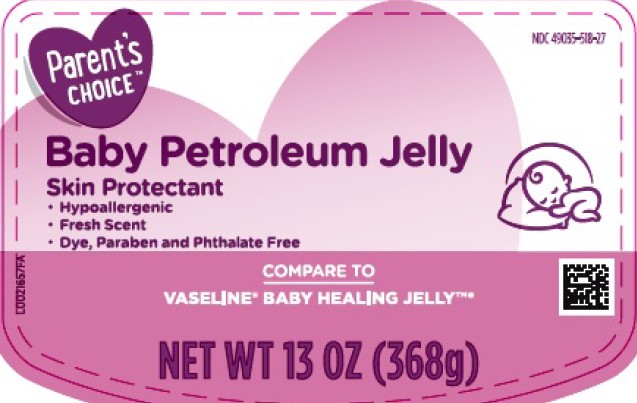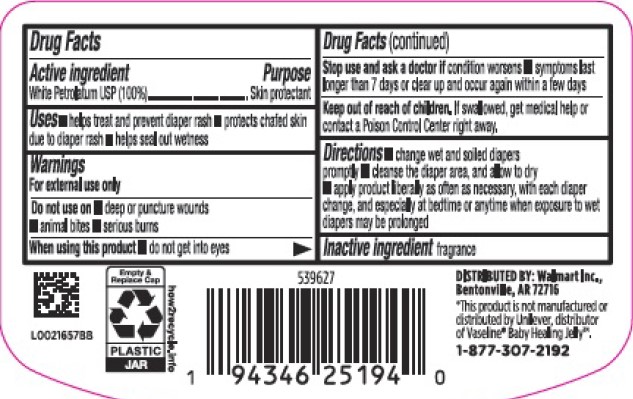 DRUG LABEL: White Petrolatum
NDC: 49035-518 | Form: JELLY
Manufacturer: Walmart Inc.
Category: otc | Type: HUMAN OTC DRUG LABEL
Date: 20260227

ACTIVE INGREDIENTS: PETROLATUM 100 g/100 g

Parent's Choice 519.001/AC-AE
Baby Petroleum Jelly

Active ingredient

White Petrolatum USP (100%)

Purpose

Skin protectant

Uses

- helps treat and prevent diaper rash
- protects chafed skin due to diaper rash
- helps seal out wetness

Warnings

For external use only

Do not use on

- deep or puncture wounds
- animal bites
- serious burns

When using this product

- do not get into eyes

Stop use and ask a doctor if condition worsens

- symptoms longer than 7 days or clear up and occur again within a few days

Keep out of reach of children.

If swallowed, get medical help or contact a Poison Control Center right away.

Directions

- change wet and soiled diapers promptly
- cleanse the diaper area, and allow to dry
- apply product liberally as often as necessary, with each diaper change, and especially at bedtime or anytime when exposure to wet diapers may be prolonged

Inactive ingredient

fragrance

Adverse reaction

DISTRIBUTED BY: Walmart Inc.

Bentonville, AR 72716

*This product is not manufactured or distributed by Unilever, distributor of Vaseline® Baby Healing Jelly™.

1-877-307-2192

Empty & Replace Cap

PLASTIC JAR

how2recycle.info

Principal display panel

Parent's Choice™

NDC 49035-518-27

Baby Petroleum Jelly

Skin Protectant

- Hypoallergenic
- Fresh Scent
- Dye, Paraben and Phthalate free

COMPARE TO VASELINE®BABY HEALING JELLY™*

NET WT 13 OZ (368 g)